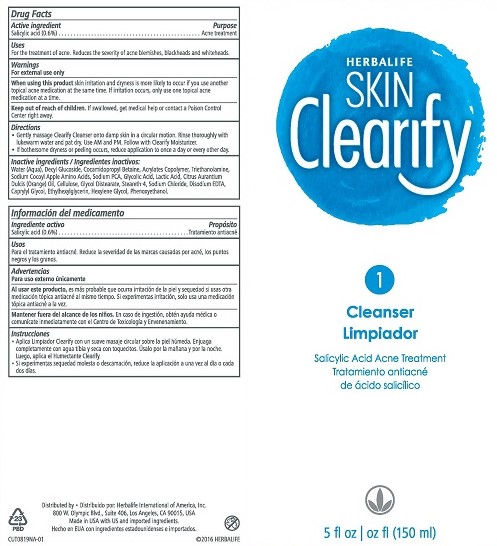 DRUG LABEL: Skin Clearify Cleanser
NDC: 51785-819 | Form: LIQUID
Manufacturer: Herbalife International of America Inc.
Category: otc | Type: HUMAN OTC DRUG LABEL
Date: 20161010

ACTIVE INGREDIENTS: SALICYLIC ACID 0.6 g/100 mL
INACTIVE INGREDIENTS: GLYCOLIC ACID; LACTIC ACID; GLYCOL DISTEARATE; COCAMIDOPROPYL BETAINE; DECYL GLUCOSIDE; PHENOXYETHANOL; WATER; ETHYLHEXYLGLYCERIN; EDETATE DISODIUM; TROLAMINE; CAPRYLYL GLYCOL; HEXYLENE GLYCOL; SODIUM PYRROLIDONE CARBOXYLATE; ORANGE OIL; POWDERED CELLULOSE; STEARETH-4; SODIUM CHLORIDE

Clearify Acne Cleanser

Drug Facts

Active ingredient

Salicylic acid (0.6%)

Purpose

Acne treatment

Uses

For the treatment of acne. Reduces the severity of acne blemishes, blackheads, and whiteheads.

Warnings

For external use only

When using this product skin irritation and dryness is more likely to occur if you use another topical acne medication at the same time. If irritation occurs, only use one topical acne medication at a time.

Keep out of reach of children. If swallowed, get medical help or contact a Poison Control Center right away.

Directions

- Gently massage Clearify Cleanser onto damp skin in a circular motion. Rinse thoroughly with lukewarm water and pat dry. Use AM and PM. Follow with Clearify Moisturizer.
- If bothersome dryness or peeling occurs, reduce application to once a day or every other day.

INACTIVE INGREDIENT

Inactive ingredients: Water (Aqua), Decyl Glucoside, Cocamidopropyl Betaine, Acrylates Copolymer, Triethanolamine, Sodium Cocoyl Apple Amino Acids, Sodium PCA, Glycolic Acid, Lactic Acid, Citrus Aurantium Dulcis (Orange) Oil, Cellulose, Glycol Distearate, Steareth-4, Sodium Chloride, Disodium EDTA, Caprylyl Glycol, Ethylhexylglycerin, Hexylene Glycol, Phenoxyethanol.

Distributed by: Herbalife International of America, Inc.

800 W. Olympic Blvd., Suite 406, Los Angeles, CA 90015 USA

Made in USA with US and imported ingredients.

© 2016 HERBALIFE

PACKAGE LABEL

HERBALIFE

SKIN Clearify

1

Cleanser

Salicylic Acid Acne Treatment

5 fl oz (150 ml)